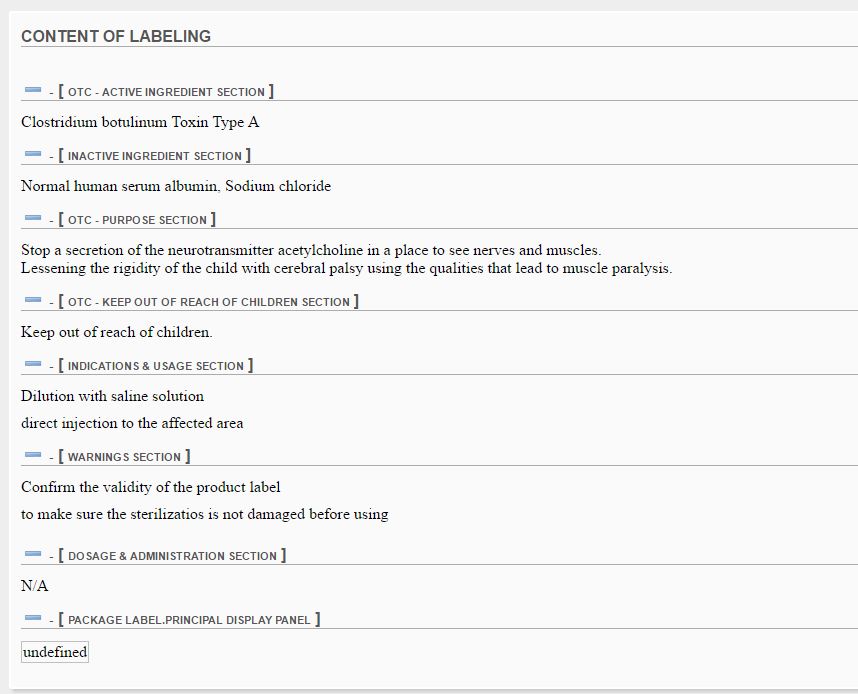 DRUG LABEL: PROTOXIN
NDC: 71066-0001 | Form: GEL
Manufacturer: PROTOX Inc.
Category: otc | Type: HUMAN OTC DRUG LABEL
Date: 20161110

ACTIVE INGREDIENTS: CLOSTRIDIUM BOTULINUM 10 g/10 mL
INACTIVE INGREDIENTS: ALBUMIN HUMAN; SODIUM CHLORIDE

ACTIVE INGREDIENT

Clostridium botulinum Toxin Type A

INACTIVE INGREDIENT

Normal human serum albumin, Sodium chloride

PURPOSE

Stop a secretion of the neurotransmitter acetylcholine in a place to see nerves and muscles.
Lessening the rigidity of the child with cerebral palsy using the qualities that lead to muscle paralysis.

Keep out of reach of children.

WARNINGS

Confirm the validity of the product label

to make sure the sterilizatios is not damaged before using

DOSAGE AND ADMINISTRATION

N/A

INDICATIONS AND USAGE

N/A